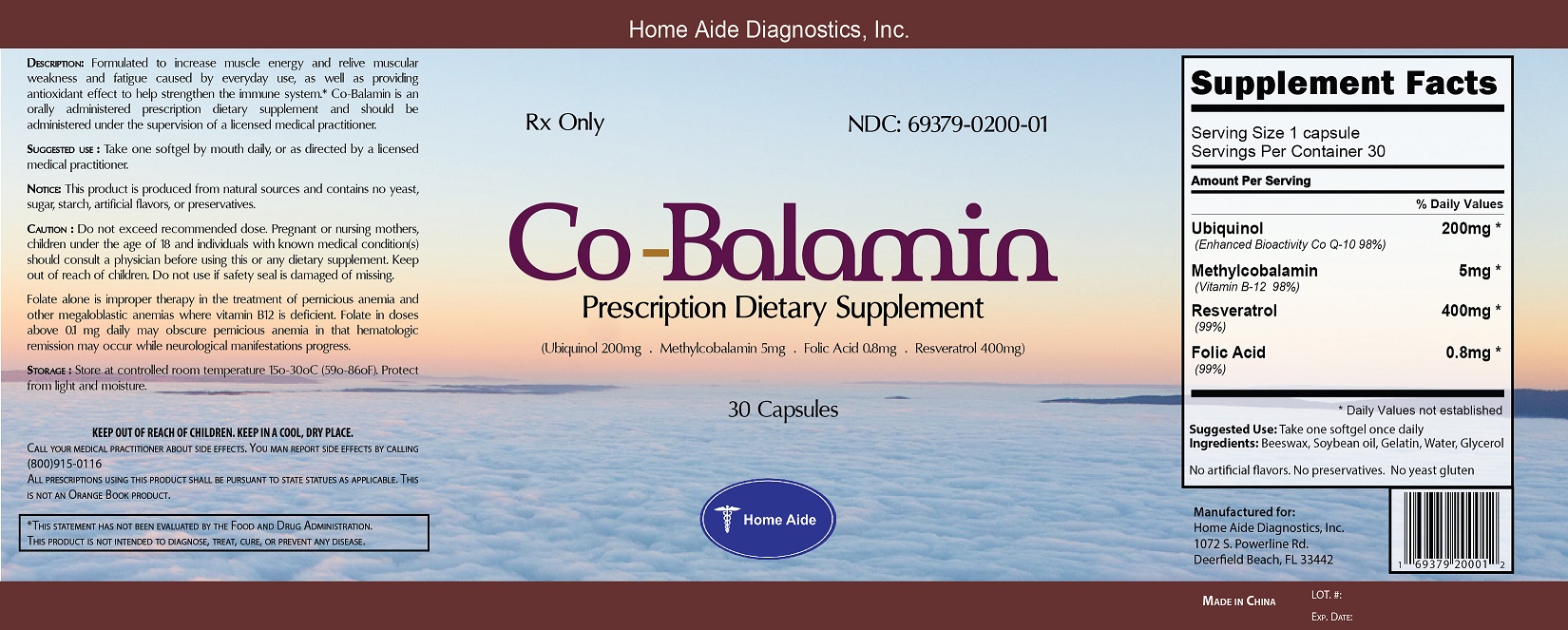 DRUG LABEL: Co-Balamin
NDC: 69379-200 | Form: CAPSULE
Manufacturer: Home Aide Diagnostics, Inc.
Category: other | Type: DIETARY SUPPLEMENT
Date: 20160128

ACTIVE INGREDIENTS: UBIQUINOL 200 mg/1 mg; METHYLCOBALAMIN 5 mg/1 mg; RESVERATROL 400 mg/1 mg; FOLIC ACID 0.8 mg/1 mg

Co-Balamin

STATEMENT OF IDENTITY

Suggested use : Take 1 capsule daily. Cardiovascular System Support┼, as a dietary supplement. This product is produced from natural sources and contains no yeast, sugar, starch, artifical flavors, or preservatives.

WARNINGS

Caution : Do not exceed recommended dose. Pregnant or nursing mothers, children under the age of 18 and individuals with known medical condition(s) should consult a physician before using this or any dietary supplement. Keep out of reach of children. Do not use if safety seal is damaged of missing.

Storage : Keep at room temperature in a dark dry place